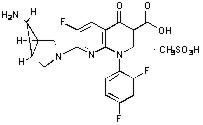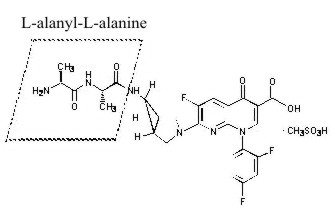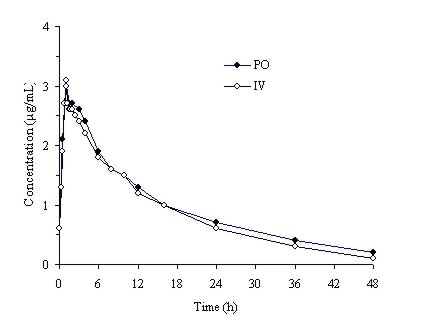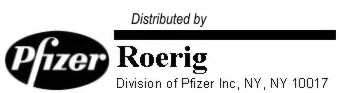 DRUG LABEL: Unknown
Manufacturer: Roerig
Category: prescription | Type: HUMAN PRESCRIPTION DRUG LABELING
Date: 20060206

TROVAN® Tablets
(trovafloxacin mesylate)
TROVAN® I.V.
(alatrofloxacin mesylate injection)
For Intravenous Infusion

BOXED WARNING

TROVAN® HAS BEEN ASSOCIATED WITH SERIOUS LIVER INJURY LEADING TO LIVER TRANSPLANTATION AND/OR DEATH. TROVAN-ASSOCIATED LIVER INJURY HAS BEEN REPORTED WITH BOTH SHORT-TERM AND LONG-TERM DRUG EXPOSURE. TROVAN USE EXCEEDING 2 WEEKS IN DURATION IS ASSOCIATED WITH A SIGNIFICANTLY INCREASED RISK OF SERIOUS LIVER INJURY. LIVER INJURY HAS ALSO BEEN REPORTED FOLLOWING TROVAN RE-EXPOSURE. TROVAN SHOULD BE RESERVED FOR USE IN PATIENTS WITH SERIOUS, LIFE- OR LIMB-THREATENING INFECTIONS WHO RECEIVE THEIR INITIAL THERAPY IN AN IN-PATIENT HEALTH CARE FACILITY (I.E., HOSPITAL OR LONG-TERM NURSING CARE FACILITY). TROVAN SHOULD NOT BE USED WHEN SAFER, ALTERNATIVE ANTIMICROBIAL THERAPY WILL BE EFFECTIVE. (SEE WARNINGS.)

TROVAN is available as TROVAN Tablets (trovafloxacin mesylate) for oral administration and as TROVAN I.V. (alatrofloxacin mesylate injection), a prodrug of trovafloxacin, for intravenous administration.

DESCRIPTION

TROVAN Tablets

TROVAN Tablets contain trovafloxacin mesylate, a synthetic broad-spectrum antibacterial agent for oral administration. Chemically, trovafloxacin mesylate, a fluoronaphthyridone related to the fluoroquinolone antibacterials, is (1α, 5α, 6α)-7-(6-amino-3-azabicyclo[3.1.0]hex-3-yl)-1-(2,4-difluorophenyl)-6-fluoro-1,4-dihydro-4-oxo-1,8-naphthyridine-3-carboxylic acid, monomethanesulfonate. Trovafloxacin mesylate differs from other quinolone derivatives by having a 1,8-naphthyridine nucleus.

The chemical structure is:

Its empirical formula is C20H15F3N4O3•CH3SO3H and its molecular weight is 512.46.

Trovafloxacin mesylate is a white to off-white powder.

Trovafloxacin mesylate is available in 100 mg and 200 mg (trovafloxacin equivalent) blue, film-coated tablets. TROVAN Tablets contain microcrystalline cellulose, cross-linked sodium carboxymethylcellulose and magnesium stearate. The tablet coating is a mixture of hydroxypropylcellulose, hydroxypropylmethylcellulose, titanium dioxide, polyethylene glycol and FD&C blue #2 aluminum lake.

TROVAN I.V. contains alatrofloxacin mesylate, the L-alanyl-L-alanyl prodrug of trovafloxacin mesylate. Chemically, alatrofloxacin mesylate is (1α, 5α, 6α)-L-alanyl-N-[3-[6-carboxy-8-(2,4-difluorophenyl)-3-fluoro-5,8-dihydro-5-oxo-1,8-naphthyridine-2-yl]-3-azabicyclo[3.1.0]hex-6-yl]-L-alaninamide, monomethanesulfonate. It is intended for administration by intravenous infusion.

Following intravenous administration, the alanine substituents in alatrofloxacin are rapidly hydrolyzed in vivo to yield trovafloxacin. (See CLINICAL PHARMACOLOGY.)

The chemical structure is:

Its empirical formula is C26H25F3N6O5•CH3SO3H and its molecular weight is 654.62.

Alatrofloxacin mesylate is a white to light yellow powder.

TROVAN I.V. is available in 40 mL and 60 mL single use vials as a sterile, preservative-free aqueous concentrate of 5 mg trovafloxacin/mL as alatrofloxacin mesylate intended for dilution prior to intravenous administration of doses of 200 mg or 300 mg of trovafloxacin, respectively. (See HOW SUPPLIED.)

The formulation contains Water for Injection, and may contain sodium hydroxide or hydrochloric acid for pH adjustment. The pH range for the 5 mg/mL aqueous concentrate is 3.5 to 4.3.

CLINICAL PHARMACOLOGY

After intravenous administration, alatrofloxacin is rapidly converted to trovafloxacin. Plasma concentrations of alatrofloxacin are below quantifiable levels within 5 to 10 minutes of completion of a 1 hour infusion.

Absorption

Trovafloxacin is well-absorbed from the gastrointestinal tract after oral administration. The absolute bioavailability is approximately 88%. For comparable dosages, no dosage adjustment is necessary when switching from parenteral to oral administration (Figure 1). (See DOSAGE AND ADMINISTRATION.)

Figure 1. Mean trovafloxacin serum concentrations determined following 1 hour intravenous infusions of alatrofloxacin at daily doses of 200 mg (trovafloxacin equivalents) to healthy male volunteers and following daily oral administration of 200 mg trovafloxacin for 7 days to six male and six female healthy young volunteers.

Pharmacokinetics

The mean pharmacokinetic parameters (±SD) of trovafloxacin after single and multiple 100 mg and 200 mg oral doses and 1 hour intravenous infusions of alatrofloxacin in doses of 200 and 300 mg (trovafloxacin equivalents) appear in the chart below.

TROVAFLOXACIN PHARMACOKINETIC PARAMETERS
 | Cmax (µg/mL) | Tmax (hrs) | AUC [Single dose: AUC(0–∞), multiple dose: AUC(0–24)] (µg•h/mL) | T½ (hrs) | Vdss (L/Kg) | CL (mL/hr/Kg) | CLr (mL/hr/Kg)
Trovafloxacin 100 mg
Single dose | 1.0±0.3 | 0.9±0.4 | 11.2±2.2 | 9.1 | — | — | —
Multiple dose | 1.1±0.2 | 1.0±0.5 | 11.8±1.8 | 10.5 | — | — | —
Trovafloxacin 200 mg
Single dose | 2.1±0.5 | 1.8±0.9 | 26.7±7.5 | 9.6 | — | — | —
Multiple dose | 3.1±1.0 | 1.2±0.5 | 34.4±5.7 | 12.2 | — | — | —
Alatrofloxacin 200 mg [trovafloxacin equivalents]
Single dose | 2.7±0.4 | 1.0±0.0 | 28.1±5.1 | 9.4 | 1.2±0.2 | 93.0±17.4 | 6.5±3.5
Multiple dose | 3.1±0.6 | 1.0±0.0 | 32.2±7.3 | 11.7 | 1.3±0.1 | 81.7±17.8 | 8.6±2.4
Alatrofloxacin 300 mg
Single dose | 3.6±0.6 | 1.3±0.4 | 46.1±5.2 | 11.2 | 1.2±0.1 | 84.6±6.0 | 6.9±0.5
Multiple dose | 4.4±0.6 | 1.2±0.2 | 46.3±3.9 | 12.7 | 1.4±0.1 | 84.5±11.1 | 8.4±1.8
Cmax=Maximum serum concentration; Tmax=Time to Cmax; AUC=Area under concentration vs. time curve; T1/2=serum half-life; Vdss=Volume of distribution; Cl=Total clearance; Clr=Renal clearance

Serum concentrations of trovafloxacin are dose proportional after oral administration of trovafloxacin in the dose range of 30 to 1000 mg or after intravenous administration of alatrofloxacin in the dose range of 30 to 400 mg (trovafloxacin equivalents). Steady state concentrations are achieved by the third daily oral or intravenous dose of trovafloxacin with an accumulation factor of approximately 1.3 times the single dose concentrations.

Oral absorption of trovafloxacin is not altered by concomitant food intake; therefore, it can be administered without regard to food.

The systemic exposure to trovafloxacin (AUC0–∞) administered as crushed tablets via nasogastric tube into the stomach was identical to that of orally administered intact tablets. Administration of concurrent enteral feeding solutions had no effect on the absorption of trovafloxacin given via nasogastric tube into the stomach. When trovafloxacin was administered as crushed tablets into the duodenum via nasogastric tube, the AUC0–∞ and peak serum concentration (Cmax) were reduced by 30% relative to the orally administered intact tablets. Time to peak serum level (Tmax) was also decreased from 1.7 hrs to 1.1 hrs.

Distribution

The mean plasma protein bound fraction is approximately 76%, and is concentration-independent. Trovafloxacin is widely distributed throughout the body. Rapid distribution of trovafloxacin into tissues results in significantly higher trovafloxacin concentrations in most target tissues than in plasma or serum.

Fluid or Tissue | Tissue-Fluid/Serum Ratio [Mean values in adults over 2–29 hours following drug administration, except individual lung tissues, which were single time points of 6 hours following drug administration] (Range)
Respiratory
bronchial macrophages (multiple dose) | 24.1 (9.6–41.8)
lung mucosa | 1.1 (0.7–1.5)
lung epithelial lining fluid (multiple dose) | 5.8 (1.1–17.5)
whole lung | 2.1 (0.42–5.03)
Skin, Musculoskeletal
skin | 1.0 (0.20–1.88)
subcutaneous tissue | 0.4 (0.15–0.68)
skin blister fluid | 0.7–0.9 (blister/plasma)
skeletal muscle | 1.5 (0.50–2.90)
bone | 1.0 (0.55–1.67)
Gastrointestinal
colonic tissue | 0.7 (0.0–1.47)
peritoneal fluid | 0.4 (0.0–1.25)
bile | 15.4 (11.9–21.0)
Central Nervous System
cerebrospinal fluid (CSF), adults | 0.25 (0.03–0.33)
cerebrospinal fluid (CSF), children | 0.28 [Ratio of composite AUC(0–24) in CSF/composite AUC(0–24) in serum in 22 pediatric patients aged 1 to 12 years after 1 hour I.V. infusion of single dose alatrofloxacin (equivalent trovafloxacin dose range: 4.5–9.9 mg/kg)]
Reproductive
prostatic tissue | 1.0 (0.5–1.6)
cervix (multiple dose) | 0.6 (0.5–0.7)
ovary | 1.6 (0.3–2.2)
fallopian tube | 0.7 (0.2–1.1)
myometrium (multiple dose) | 0.6 (0.4–0.8)
uterus | 0.6 (0.3–0.8)
vaginal fluid (multiple dose) | 4.7 (0.8–20.8)

Presence in Breast Milk

Trovafloxacin was found in measurable concentrations in the breast milk of three lactating subjects. The average measurable breast milk concentration was 0.8 µg/mL (range: 0.3–2.1 µg/mL) after single I.V. alatrofloxacin (300 mg trovafloxacin equivalents) and repeated oral trovafloxacin (200 mg) doses.

Metabolism

Trovafloxacin is metabolized by conjugation (the role of cytochrome P450 oxidative metabolism of trovafloxacin is minimal). Thirteen percent of the administered dose appears in the urine in the form of the ester glucuronide and 9% appears in the feces as the N-acetyl metabolite (2.5% of the dose is found in the serum as the active N-acetyl metabolite). Other minor metabolites (diacid, sulfamate, hydroxycarboxylic acid) have been identified in both urine and feces in small amounts (<4% of the administered dose).

Excretion

Approximately 50% of an oral dose is excreted unchanged (43% in the feces and 6% in the urine).

After multiple 200 mg doses, to healthy subjects, mean (±SD) cumulative urinary trovafloxacin concentrations were 12.1±3.4 µg/mL. With these levels of trovafloxacin in urine, crystals of trovafloxacin have not been observed in the urine of human subjects.

Special Populations

Geriatric

In adult subjects, the pharmacokinetics of trovafloxacin are not affected by age (range 19–78 years).

Pediatric

Limited information is available in the pediatric population (see Distribution). The pharmacokinetics of trovafloxacin have not been fully characterized in pediatric populations less than 18 years of age.

Gender

There are no significant differences in trovafloxacin pharmacokinetics between males and females when differences in body weight are taken into account. After single 200 mg doses, trovafloxacin Cmax and AUC(0–∞) were 60% and 32% higher, respectively, in healthy females compared to healthy males. Following repeated daily administration of 200 mg for 7 days, the Cmax for trovafloxacin was 38% higher and AUC(0–24) was 16% higher in healthy females compared to healthy males. The clinical importance of the increases in serum levels of trovafloxacin in females has not been established. (See PRECAUTIONS: Information for Patients.)

Chronic Hepatic Disease

Following repeated administration of 100 mg for 7 days to patients with mild cirrhosis (Child-Pugh Class A), the AUC(0–24) for trovafloxacin was increased ~45% compared to matched controls. Repeated administration of 200 mg for 7 days to patients with moderate cirrhosis (Child-Pugh Class B) resulted in an increase of ~50% in AUC(0–24) compared to matched controls. There appeared to be no significant effect on trovafloxacin Cmax for either group. The oral clearance of trovafloxacin was reduced ~30% in both cirrhosis groups, which corresponded to prolongation of half life by 2–2.5 hours (25–30% increase) compared to controls. There are no data in patients with severe cirrhosis (Child-Pugh Class C). Dosage adjustment is recommended in patients with mild to moderate cirrhosis. (See DOSAGE AND ADMINISTRATION.)

Renal Insufficiency

The pharmacokinetics of trovafloxacin are not affected by renal impairment. Trovafloxacin serum concentrations are not significantly altered in subjects with severe renal insufficiency (creatinine clearance <20 mL/min), including patients on hemodialysis.

Photosensitivity Potential

In a study of the skin response to ultraviolet and visible radiation conducted in 48 healthy volunteers (12 per group), the minimum erythematous dose (MED) was measured for ciprofloxacin, lomefloxacin, trovafloxacin and placebo before and after drug administration for 5 days. In this study, trovafloxacin (200 mg q.d.) was shown to have a lower potential for producing delayed photosensitivity skin reactions than ciprofloxacin (500 mg b.i.d.) or lomefloxacin (400 mg q.d.), although greater than placebo. (See PRECAUTIONS: Information for Patients.)

Drug-drug Interactions

The systemic availability of trovafloxacin following oral tablet administration is significantly reduced by the concomitant administration of antacids containing aluminum and magnesium salts, sucralfate, vitamins or minerals containing iron, and concomitant intravenous morphine administration.

Administration of trovafloxacin (300 mg p.o.) 30 minutes after administration of an antacid containing magnesium hydroxide and aluminum hydroxide resulted in reductions in systemic exposure to trovafloxacin (AUC) of 66% and peak serum concentration (Cmax) of 60%. (See PRECAUTIONS: Drug Interactions, DOSAGE AND ADMINISTRATION.)

Concomitant sucralfate administration (1g) with trovafloxacin 200 mg p.o. resulted in a 70% decrease in trovafloxacin systemic exposure (AUC) and a 77% reduction in peak serum concentration (Cmax). (See PRECAUTIONS: Drug Interactions, DOSAGE AND ADMINISTRATION.)

Concomitant administration of ferrous sulfate (120 mg elemental iron) with trovafloxacin 200 mg p.o. resulted in a 40% reduction in trovafloxacin systemic exposure (AUC) and a 48% decrease in trovafloxacin Cmax. (See PRECAUTIONS: Drug Interactions, DOSAGE AND ADMINISTRATION.)

Concomitant administration of intravenous morphine (0.15 mg/kg) with oral trovafloxacin (200 mg) resulted in a 36% reduction in trovafloxacin AUC and a 46% decrease in trovafloxacin Cmax. Trovafloxacin administration had no effect on the pharmacokinetics of morphine or its pharmacologically active metabolite, morphine-6-β-glucuronide. (See PRECAUTIONS: Drug Interactions, DOSAGE AND ADMINISTRATION.)

Minor pharmacokinetic interactions that are most likely without clinical significance include calcium carbonate, omeprazole and caffeine.

Concomitant administration of calcium carbonate (1000 mg) with trovafloxacin 200 mg p.o. resulted in a 20% reduction in trovafloxacin AUC and a 17% reduction in peak serum trovafloxacin concentration (Cmax).

A 40 mg dose of omeprazole given 2 hours prior to trovafloxacin (300 mg p.o.) resulted in a 17% reduction in trovafloxacin AUC and a 17% reduction in trovafloxacin peak serum concentration (Cmax).

Administration of trovafloxacin (200 mg) concomitantly with caffeine (200 mg) resulted in a 17% increase in caffeine AUC and a 15% increase in caffeine Cmax. These changes in caffeine exposure are not considered clinically significant.

No significant pharmacokinetic interactions were seen when TROVAN was co-administered with cimetidine, theophylline, digoxin, warfarin and cyclosporine.

Cimetidine co-administration (400 mg twice daily for 5 days) with trovafloxacin (200 mg p.o. daily for 3 days) resulted in changes in trovafloxacin AUC and Cmax of less than 5%.

Trovafloxacin (200 mg p.o. daily for 7 days) co-administration with theophylline (300 mg twice daily for 14 days) resulted in no change in theophylline AUC and Cmax.

Trovafloxacin (200 mg p.o. daily for 10 days) co-administration with digoxin (0.25 mg daily for 20 days) did not significantly alter systemic exposure (AUC) to digoxin or the renal clearance of digoxin.

Trovafloxacin (200 mg p.o. daily for 7 days) did not interfere with either the pharmacokinetics or the pharmacodynamics of warfarin (daily for 21 days).

Concomitant oral administration of trovafloxacin did not affect the systemic exposure (AUC) or peak plasma concentrations (Cmax) of the S or R isomers of warfarin, nor did it influence prothrombin times. (See PRECAUTIONS: Drug Interactions.)

Trovafloxacin (200 mg p.o. daily for 7 days) co-administration with cyclosporine (daily doses from 150–450 mg for 7 days) resulted in decreases of 10% or less in systemic exposure to cyclosporine (AUC) and in the peak blood concentrations of cyclosporine.

Microbiology

Trovafloxacin is a fluoronaphthyridone related to the fluoroquinolones with in vitro activity against a wide range of gram-negative and gram-positive aerobic, and anaerobic microorganisms. The bactericidal action of trovafloxacin results from inhibition of DNA gyrase and topoisomerase IV. DNA gyrase is an essential enzyme that is involved in the replication, transcription and repair of bacterial DNA. Topoisomerase IV is an enzyme known to play a key role in the partitioning of the chromosomal DNA during bacterial cell division. Mechanism of action of fluoroquinolones including trovafloxacin is different from that of penicillins, cephalosporins, aminoglycosides, macrolides, and tetracyclines. Therefore, fluoroquinolones may be active against pathogens that are resistant to these antibiotics. There is no cross-resistance between trovafloxacin and the mentioned classes of antibiotics. The overall results obtained from in vitro synergy studies, testing combinations of trovafloxacin with beta-lactams and aminoglycosides, indicate that synergy is strain specific and not commonly encountered. This agrees with results obtained previously with other fluoroquinolones. Resistance to trovafloxacin in vitro develops slowly via multiple-step mutation in a manner similar to other fluoroquinolones. Resistance to trovafloxacin in vitro occurs at a general frequency of between 1×10^-7 to 10^-10. Although cross-resistance has been observed between trovafloxacin and some other fluoroquinolones, some microorganisms resistant to other fluoroquinolones may be susceptible to trovafloxacin.

Trovafloxacin has been shown to be active against most strains of the following microorganisms, both in vitro and in clinical infections as described in the INDICATIONS AND USAGE section:

Aerobic gram-positive microorganisms
Enterococcus faecalis (many strains are only moderately susceptible)
Staphylococcus aureus (methicillin-susceptible strains)
Streptococcus agalactiae
Streptococcus pneumoniae (penicillin-susceptible strains)
Viridans group streptococci

Aerobic gram-negative microorganisms
Escherichia coli
Gardnerella vaginalis
Haemophilus influenzae
Klebsiella pneumoniae
Moraxella catarrhalis
Proteus mirabilis
Pseudomonas aeruginosa

Anaerobic microorganisms
Bacteroides fragilis
Peptostreptococcus species
Prevotella species

Other microorganisms
Chlamydia pneumoniae
Legionella pneumophila
Mycoplasma pneumoniae

The following in vitro data are available, but their clinical significance is unknown.

Trovafloxacin exhibits in vitro minimum inhibitory concentrations (MICs) of ≤2 µg/mL against most (90%) strains of the following microorganisms; however, the safety and effectiveness of trovafloxacin in treating clinical infections due to these microorganisms have not been established in adequate and well-controlled clinical trials.

Aerobic gram-positive microorganisms
Streptococcus pneumoniae (penicillin resistant strains)

Aerobic gram-negative microorganisms
Citrobacter freundii
Enterobacter aerogenes
Morganella morganii
Proteus vulgaris

Anaerobic microorganisms
Bacteroides distasonis
Bacteroides ovatus
Clostridium perfringens

Other microorganisms
Mycoplasma hominis
Ureaplasma urealyticum

NOTE: Mycobacterium tuberculosis and Mycobacterium avium-intracellulare complex organisms are commonly resistant to trovafloxacin.

NOTE: The activity of trovafloxacin against Treponema pallidum has not been evaluated; however, other quinolones are not active against Treponema pallidum. (See WARNINGS.)

Susceptibility Tests

Dilution Techniques: Quantitative methods are used to determine antimicrobial minimum inhibitory concentrations (MICs). These MICs provide estimates of the susceptibility of bacteria to antimicrobial compounds. The MICs should be determined using a standardized procedure. Standardized procedures are based on dilution methods^1 (broth or agar) or equivalent with standardized inoculum concentrations and standardized concentrations of trovafloxacin mesylate powder. The MIC values should be interpreted according to the following criteria:

For testing non-fastidious aerobic organisms:

MIC (µg/mL) | Interpretation
≤2.0 | Susceptible (S)
4.0 | Intermediate (I)
≥8.0 | Resistant (R)

For testing Haemophilus spp. [This interpretive standard is applicable only to broth microdilution susceptibility tests with Haemophilus spp. using Haemophilus Test Medium (HTM)^1.]

MIC (µg/mL) | Interpretation [The current absence of data on resistant strains precludes defining any results other than "Susceptible". Strains yielding MIC results suggestive of a "nonsusceptible" category should be submitted to a reference laboratory for further testing.]
≤1.0 | Susceptible (S)

For testing Streptococcus spp. including Streptococcus pneumoniae [These interpretive standards are applicable only to broth microdilution susceptibility tests using cation adjusted Mueller-Hinton broth with 2–5% lysed horse blood.] :

MIC (µg/mL) | Interpretation
≤1.0 | Susceptible (S)
2.0 | Intermediate (I)
≥4.0 | Resistant (R)

A report of "Susceptible" indicates that the pathogen is likely to be inhibited if the antimicrobial compound in the blood reaches the concentration usually achievable. A report of "Intermediate" indicates that the result should be considered equivocal, and, if the microorganism is not fully susceptible to alternative, clinically feasible drugs, the test should be repeated. This category implies possible clinical applicability in body sites where the drug is physiologically concentrated or in situations where high dosage of drug can be used. This category also provides a buffer zone which prevents small uncontrolled technical factors from causing major discrepancies in interpretation. A report of "Resistant" indicates that the pathogen is not likely to be inhibited if the antimicrobial compound in the blood reaches the concentration usually achievable; other therapy should be selected.

Standardized susceptibility test procedures require the use of laboratory control microorganisms to control the technical aspects of the laboratory procedures. Standard trovafloxacin mesylate powder should provide the following MIC values:

Microorganism | MIC Range (µg/mL)
Escherichia coli ATCC 25922 | 0.004–0.016
Staphylococcus aureus ATCC 29213 | 0.008–0.03
Pseudomonas aeruginosa ATCC 27853 | 0.25–2.0
Enterococcus faecalis ATCC 29212 | 0.06–0.25
Haemophilus influenzae [This quality control range is applicable to only H. influenzae ATCC 49247 tested by a microdilution procedure using HTM^1.] ATCC 49247 | 0.004–0.016
Streptococcus pneumoniae [This quality control range is applicable to only S. pneumoniae ATCC 49619 tested by a microdilution procedure using cation-adjusted Mueller-Hinton broth with 2–5% lysed horse blood.] ATCC 49619 | 0.06–0.25

Diffusion Techniques: Quantitative methods that require measurement of zone diameters also provide reproducible estimates of the susceptibility of bacteria to antimicrobial compounds. One such standardized procedure^2 requires the use of standardized inoculum concentrations. This procedure uses paper disks impregnated with trovafloxacin mesylate equivalent to 10 µg trovafloxacin to test the susceptibility of microorganisms to trovafloxacin.

Reports from the laboratory providing results of the standard single-disk susceptibility test with a trovafloxacin mesylate disk (equivalent to 10 µg trovafloxacin) should be interpreted according to the following criteria:

The following zone diameter interpretive criteria should be used for testing non-fastidious aerobic organisms:

Zone Diameter (mm) | Interpretation
≥17 | Susceptible (S)
14–16 | Intermediate (I)
≤13 | Resistant (R)

For testing Haemophilus spp. [This zone diameter standard is applicable only to tests with Haemophilus spp. using HTM^2.] :

Zone Diameter (mm) | Interpretation [The current absence of data on resistant strains precludes defining any results other than "Susceptible". Strains yielding MIC results suggestive of a "nonsusceptible" category should be submitted to a reference laboratory for further testing.]
≥22 | Susceptible (S)

For testing Streptococcus spp. including Streptococcus pneumoniae [These zone diameter standards only apply to tests performed using Mueller-Hinton agar supplemented with 5% sheep blood incubated in 5% CO2.] :

Zone Diameter (mm) | Interpretation
≥19 | Susceptible (S)
18–16 | Intermediate (I)
≤15 | Resistant (R)

Interpretation should be as stated above for results using dilution techniques. Interpretation involves correlation of the diameter obtained in the disk test with the MIC for trovafloxacin.

As with standardized dilution techniques, diffusion methods require the use of laboratory control microorganisms that are used to control the technical aspects of the laboratory procedures. For the diffusion technique, the trovafloxacin mesylate equivalent to 10-µg trovafloxacin disk should provide the following zone diameters in these laboratory quality control strains:

Microorganism | Zone Diameter Range (mm)
Escherichia coli ATCC 25922 | 29–36
Staphylococcus aureus ATCC 25923 | 29–35
Pseudomonas aeruginosa ATCC 27853 | 21–27
Haemophilus influenzae [This quality control limit applies to tests conducted with Haemophilus influenzae ATCC 49247 using HTM^2.] ATCC 49247 | 32–39
Streptococcus pneumoniae [This quality control range is applicable only to tests performed by disk diffusion using Mueller-Hinton agar supplemented with 5% defibrinated sheep blood.] ATCC 49619 | 25–32

Anaerobic Techniques: For anaerobic bacteria, the susceptibility to trovafloxacin as MICs can be determined by standardized test methods^3. The MIC values obtained should be interpreted according to the following criteria:

MIC (µg/mL) | Interpretation
≤2.0 | Susceptible (S)
4.0 | Intermediate (I)
≥8.0 | Resistant (R)

Interpretation is identical to that stated above for results using dilution techniques.

As with other susceptibility techniques, the use of laboratory control microorganisms is required to control the technical aspects of the laboratory standardized procedures. Standardized trovafloxacin mesylate powder should provide the following MIC values:

Microorganism | MIC [kThese quality control ranges were derived from tests performed in the broth formulation of Wilkins-Chalgren agar.] (µg/mL)
Bacteroides fragilis ATCC 25285 | 0.125–0.5
Bacteroides thetaiotamicron ATCC 29741 | 0.25–1.0
Eubacterium lentum ATCC 43055 | 0.25–1.0

INDICATIONS AND USAGE

TROVAN is indicated for the treatment of patients initiating therapy in in-patient health care facilities (i.e., hospitals and long term nursing care facilities) with serious, life- or limb-threatening infections caused by susceptible strains of the designated microorganisms in the conditions listed below. (See DOSAGE AND ADMINISTRATION.)

Nosocomial pneumonia caused by Escherichia coli, Pseudomonas aeruginosa, Haemophilus influenzae, or Staphylococcus aureus. As with other antimicrobials, where Pseudomonas aeruginosa is a documented or presumptive pathogen, combination therapy with either an aminoglycoside or aztreonam may be clinically indicated.

Community acquired pneumonia caused by Streptococcus pneumoniae, Haemophilus influenzae, Klebsiella pneumoniae, Staphylococcus aureus, Mycoplasma pneumoniae, Moraxella catarrhalis, Legionella pneumophila, or Chlamydia pneumoniae.

Complicated intra-abdominal infections, including post-surgical infections caused by Escherichia coli, Bacteroides fragilis, viridans group streptococci, Pseudomonas aeruginosa, Klebsiella pneumoniae, Peptostreptococcus species, or Prevotella species.

Gynecologic and pelvic infections including endomyometritis, parametritis, septic abortion and post-partum infections caused by Escherichia coli, Bacteroides fragilis, viridans group streptococci, Enterococcus faecalis, Streptococcus agalactiae, Peptostreptococcus species, Prevotella species, or Gardnerella vaginalis.

Complicated skin and skin structure infections, including diabetic foot infections, caused by Staphylococcus aureus, Streptococcus agalactiae, Pseudomonas aeruginosa, Enterococcus faecalis, Escherichia coli, or Proteus mirabilis. NOTE: TROVAN has not been studied in the treatment of osteomyelitis. (See WARNINGS.)

CONTRAINDICATIONS

TROVAN is contraindicated in persons with a history of hypersensitivity to trovafloxacin, alatrofloxacin, quinolone antimicrobial agents or any other components of these products.

WARNINGS

(See boxed WARNING.) TROVAN-ASSOCIATED LIVER ENZYME ABNORMALITIES, SYMPTOMATIC HEPATITIS, JAUNDICE, AND LIVER FAILURE (INCLUDING RARE REPORTS OF ACUTE HEPATIC NECROSIS WITH EOSINOPHILIC INFILTRATION, LIVER TRANSPLANTATION AND/OR DEATH) HAVE BEEN REPORTED WITH BOTH SHORT-TERM AND LONG-TERM DRUG EXPOSURE IN MEN AND WOMEN. TROVAN USE EXCEEDING 2 WEEKS IN DURATION IS ASSOCIATED WITH A SIGNIFICANTLY INCREASED RISK OF SERIOUS LIVER INJURY. LIVER INJURY HAS ALSO BEEN REPORTED FOLLOWING TROVAN RE-EXPOSURE. CLINICIANS SHOULD MONITOR LIVER FUNCTION TESTS (e.g., AST, ALT, BILIRUBIN) IN TROVAN RECIPIENTS WHO DEVELOP SIGNS OR SYMPTOMS CONSISTENT WITH HEPATITIS. CLINICIANS SHOULD CONSIDER DISCONTINUING TROVAN IN THOSE PATIENTS WHO DEVELOP LIVER FUNCTION TEST ABNORMALITIES.

THE SAFETY AND EFFECTIVENESS OF TROVAFLOXACIN IN PEDIATRIC PATIENTS AND ADOLESCENTS LESS THAN 18 YEARS OF AGE, PREGNANT WOMEN, AND NURSING WOMEN HAVE NOT BEEN ESTABLISHED. (See PRECAUTIONS: Pediatric Use, Pregnancy, and Nursing Mothers subsections.)

As with other members of the quinolone class, trovafloxacin has caused arthropathy and/or chondrodysplasia in immature rats and dogs. The significance of these findings to humans is unknown. (See ANIMAL PHARMACOLOGY.)

Convulsions, increased intracranial pressure and psychosis have been reported in patients receiving quinolones. Quinolones may also cause central nervous system stimulation which may lead to tremors, restlessness, lightheadedness, confusion, hallucinations, paranoia, depression, nightmares and insomnia. These reactions may occur following the first dose. If these reactions occur in patients receiving trovafloxacin or alatrofloxacin, the drug should be discontinued and appropriate measures instituted. (See PRECAUTIONS: General,Information for Patients, Drug Interactions and ADVERSE REACTIONS.)

As with other quinolones, TROVAN should be used with caution in patients with known or suspected CNS disorders, such as severe cerebral atherosclerosis, epilepsy, and other factors that predispose to seizures. (See ADVERSE REACTIONS.)

Serious and occasionally fatal hypersensitivity and/or anaphylactic reactions have been reported in patients receiving therapy with TROVAN. These reactions may occur following the first dose. Some reactions have been accompanied by cardiovascular collapse, hypotension/shock, seizure, loss of consciousness, tingling, angioedema (including tongue, laryngeal, throat or facial edema/swelling), airway obstruction (including bronchospasm, shortness of breath and acute respiratory distress), dyspnea, urticaria, itching and other serious skin reactions, including generalized erythema.

Life-threatening hypotension has been reported with alatrofloxacin administration. This has occurred in patients receiving alatrofloxacin at either the recommended rate of infusion or if given more rapidly. Hypotension may be potentiated with the concomitant administration of anesthetic agents. Alatrofloxacin should only be administered by slow intravenous infusion over a period of 60 minutes. Blood pressure should be monitored closely during infusion.

TROVAN should be discontinued at the first appearance of a skin rash or any other sign of hypersensitivity. Serious acute hypersensitivity reactions may require treatment with epinephrine and other resuscitative measures, including oxygen, intravenous fluids, antihistamines, corticosteroids, pressor amines and airway management, as clinically indicated. (See PRECAUTIONS and ADVERSE REACTIONS.)

Serious and sometimes fatal events, some due to hypersensitivity and some due to uncertain etiology, have been reported in patients receiving therapy with all antibiotics. These events may be severe and generally occur following the administration of multiple doses. Clinical manifestations may include one or more of the following: fever, rash or severe dermatologic reactions (e.g., toxic epidermal necrolysis, Stevens-Johnson Syndrome); vasculitis, arthralgia, myalgia, serum sickness; allergic pneumonitis, interstitial nephritis; acute renal insufficiency or failure; hepatitis, jaundice, acute hepatic necrosis or failure; anemia, including hemolytic and aplastic; thrombocytopenia, including thrombotic thrombocytopenic purpura; leukopenia; agranulocytosis; pancytopenia; and/or other hematologic abnormalities.

Pseudomembranous colitis has been reported with nearly all antibacterial agents, including TROVAN, and may range in severity from mild to life-threatening. Therefore, it is important to consider this diagnosis in patients who present with diarrhea subsequent to the administration of any antibacterial agent.

Treatment with antibacterial agents alters the flora of the colon and may permit overgrowth of clostridia. Studies indicate that a toxin produced by Clostridium difficile is the primary cause of "antibiotic-associated colitis."

After the diagnosis of pseudomembranous colitis has been established, therapeutic measures should be initiated. Mild cases of pseudomembranous colitis usually respond to drug discontinuation alone. In moderate to severe cases, consideration should be given to management with fluids and electrolytes, protein supplementation, and treatment with an antibacterial drug clinically effective against C. difficile colitis. (See ADVERSE REACTIONS.)

Although not seen in TROVAN clinical trials, ruptures of the shoulder, hand, and Achilles tendons that required surgical repair or resulted in prolonged disability have been reported in patients receiving quinolones. TROVAN should be discontinued if the patient experiences pain, inflammation or rupture of a tendon. Patients should rest and refrain from exercise until the diagnosis of tendinitis or tendon rupture has been confidently excluded. Tendon rupture can occur during or after therapy with quinolones.

Trovafloxacin has not been shown to be effective in the treatment of syphilis. Antimicrobial agents used in high doses for short periods of time to treat gonorrhea may mask or delay the symptoms of incubating syphilis. All patients with gonorrhea should have a serologic test for syphilis at the time of diagnosis.

PRECAUTIONS

General

Moderate to severe phototoxicity reactions have been observed in patients who are exposed to direct sunlight while receiving some drugs in this class. Therapy should be discontinued if phototoxicity (e.g., a skin eruption, etc.) occurs.

The safety and efficacy of TROVAN in patients with severe cirrhosis (Child-Pugh Class C) have not been studied.

Symptomatic pancreatitis has been reported on therapy. Clinicians should monitor pancreatic tests in patients who develop symptoms consistent with pancreatitis as clinically indicated.

Because a rapid or bolus intravenous injection may result in life-threatening hypotension, alatrofloxacin should only be administered by slow intravenous infusion over a period of 60 minutes. Profound hypotension has also been reported in patients receiving alatrofloxacin at the recommended rate of infusion. (See WARNINGS and DOSAGE AND ADMINISTRATION: Intravenous Administration.)

Information For Patients

Patients should be advised:

- to discontinue therapy and to inform their physician immediately if they develop symptoms suggestive of hepatic dysfunction including fatigue, anorexia, vomiting, abdominal pain, jaundice, dark urine or pale stool. (See WARNINGS.)
- to inform their physician if they develop symptoms suggestive of pancreatitis including abdominal pain and/or nausea and vomiting. (See PRECAUTIONS: General.)
- that TROVAN Tablets may be taken without regard to meals;
- that vitamins or minerals containing iron, aluminum- or magnesium-base antacids, antacids containing citric acid buffered with sodium citrate, or sucralfate or Videx®, (Didanosine), chewable/buffered tablets or the pediatric powder for oral solution, should be taken at least 2 hours before or 2 hours after taking TROVAN tablets. (See PRECAUTIONS: Drug Interactions.);
- that TROVAN may cause lightheadedness and/or dizziness. Dizziness and/or lightheadedness was the most common adverse reaction reported, and for females under 45 years, it was reported significantly more frequently than in other groups. The incidence of dizziness may be substantially reduced if TROVAN Tablets are taken at bedtime or with food. Patients should know how they react to trovafloxacin before they operate an automobile or machinery or engage in activities requiring mental alertness and coordination. (See WARNINGS and ADVERSE REACTIONS.);
- to discontinue treatment and inform their physician if they experience pain, inflammation or rupture of a tendon, and to rest and refrain from exercise until the diagnosis of tendinitis or tendon rupture has been confidently excluded;
- that TROVAN may be associated with hypersensitivity reactions, even following the first dose, and to discontinue the drug at the first sign of a skin rash, hives or other skin reactions, difficulty in swallowing or breathing, any swelling suggesting angioedema (e.g., swelling of the lips, tongue, face, tightness of the throat, hoarseness), or other symptoms of an allergic reaction. (See WARNINGS and ADVERSE REACTIONS.);
- to avoid excessive sunlight or artificial ultraviolet light (e.g., tanning beds) while taking TROVAN and to discontinue therapy if phototoxicity (e.g., sunburn-like reaction or skin eruption) occurs.
- that convulsions have been reported in patients taking quinolones, including trovafloxacin, and to notify their physician before taking this drug if there is a history of this condition

Drug Interactions

Antacids, Sucralfate, and Iron: The absorption of oral trovafloxacin is significantly reduced by the concomitant administration of some antacids containing magnesium or aluminum, citric acid/sodium citrate (Bicitra®), as well as sucralfate and iron (ferrous ions). These agents as well as formulations containing divalent and trivalent cations such as Videx®, (Didanosine), chewable/buffered tablets or the pediatric powder for oral solution, should be taken at least 2 hours before or 2 hours after oral trovafloxacin administration. (See CLINICAL PHARMACOLOGY.)

Morphine: Co-administration of intravenous morphine significantly reduces the absorption of oral trovafloxacin. Intravenous morphine should be administered at least 2 hours after oral TROVAN dosing in the fasted state and at least 4 hours after oral TROVAN is taken with food. Trovafloxacin administration had no effect on the pharmacokinetics of morphine or its metabolite, morphine-6-β-glucuronide. (See CLINICAL PHARMACOLOGY.)

Warfarin: There have been reports during the post-marketing experience that trovafloxacin/alatrofloxacin enhance the effects of warfarin, including cases of bleeding. The mechanism for this reaction is unknown. Prothrombin time, International Normalized Ratio (INR) or other suitable anticoagulation tests should be closely monitored if trovafloxacin/alatrofloxacin is administered concomitantly with warfarin. Patients should also be monitored for evidence of bleeding.

Minor pharmacokinetic interactions without clinical significance have been observed with co-administration of TROVAN Tablets with caffeine, omeprazole and calcium carbonate. (See CLINICAL PHARMACOLOGY.)

No significant pharmacokinetic interactions with theophylline, cimetidine, digoxin, warfarin, or cyclosporine have been observed with TROVAN Tablets. (See CLINICAL PHARMACOLOGY.)

Alatrofloxacin should not be co-administered with any solution containing multivalent cations, e.g., magnesium, through the same intravenous line. (See DOSAGE AND ADMINISTRATION.)

Laboratory Test Interactions

There are no reported laboratory test interactions.

Carcinogenesis, Mutagenesis, Impairment Of Fertility

Long term studies in animals to determine the carcinogenic potential of trovafloxacin or alatrofloxacin have not been conducted.

TROVAN did not shorten the time to development of UV-induced skin tumors in hairless albino (Skh-1) mice; thus, it was not photo co-carcinogenic in this model. These mice received oral trovafloxacin and concurrent irradiation with simulated sunlight 5 days per week for 40 weeks followed by a 12-week treatment-free observation period. The daily dose of UV radiation used in this study was approximately 30% of the minimal dose of UV radiation that would induce erythema in Caucasian humans. The median time to the development of skin tumors in the hairless mice (42–43 weeks) was similar in the vehicle control group and those given 10 or 30 mg/kg of trovafloxacin daily. At a dose level of 30 mg/kg/day, the mice had skin trovafloxacin concentrations of approximately 7 µg/g. Following multiple 200 mg daily doses of trovafloxacin, the amount in human skin is estimated to be about 3 µg/g, based upon plasma concentrations measured at this dose level.

Trovafloxacin was not mutagenic in the Ames Salmonella reversion assay or CHO/HGPRT mammalian cell gene mutation assay and it was not clastogenic in mitogen-stimulated human lymphocytes or mouse bone marrow cells. A mouse micronucleus test conducted with alatrofloxacin was also negative. The positive response observed in the E. coli bacterial mutagenicity assay may be due to the inhibition of DNA gyrase by trovafloxacin.

Trovafloxacin and alatrofloxacin did not affect the fertility of male or female rats at oral and I.V. doses of 75 mg/kg/day and 50 mg/kg/day, respectively. These doses are 15 and 10 times the recommended maximum human dose based on mg/kg or approximately 2 times based on mg/m^2. However, oral doses of trovafloxacin at 200 mg/kg/day (40 times the recommended maximum human dose based on mg/kg or about 6 times based on mg/m^2) were associated with increased preimplantation loss in rats.

Pregnancy

Teratogenic Effects

Pregnancy Category C

An increase in skeletal variations was observed in rat fetuses after daily oral 75 mg/kg maternal doses of trovafloxacin (approximately 15 times the highest recommended human dose based on mg/kg or 2 times based upon body surface area) were administered during organogenesis. However, fetal skeletal variations were not observed in rats dosed orally with 15 mg/kg trovafloxacin. Evidence of fetotoxicity (increased perinatal mortality and decreased body weights) was also observed in rats at 75 mg/kg. Daily oral doses of trovafloxacin at 45 mg/kg (approximately 9 times the highest recommended human dose based on mg/kg or 2.7 times based upon body surface area) in the rabbit were not associated with an increased incidence of fetal skeletal variations or malformations.

An increase in skeletal variations and malformations was observed in rat fetuses after daily intravenous doses of alatrofloxacin at ≥20 mg/kg/day (approximately 4 times the highest recommended human dose based on mg/kg or 0.6 times based upon body surface area) were administered to dams during organogenesis. In the rabbit, an increase in fetal skeletal malformations was also observed when 20 mg/kg/day (approximately equal to the highest recommended human dose based upon body surface area) of alatrofloxacin was given intravenously during the period of organogenesis. Intravenous dosing of alatrofloxacin at 6.5 mg/kg in the rat or rabbit was not associated with an increased incidence of skeletal variations or malformations. Fetotoxicity and fetal skeletal malformations have been associated with other quinolones.

Oral doses of trovafloxacin >5mg/kg were associated with an increased gestation time in rats, and several dams at 75 mg/kg experienced uterine dystocia.

There are no adequate and well-controlled studies in pregnant women. TROVAN should be used during pregnancy only if the potential benefit justifies the potential risk to the fetus. (See WARNINGS.)

Nursing Mothers

Trovafloxacin is excreted in human milk and was found in measurable concentrations in the breast milk of lactating subjects. (See CLINICAL PHARMACOLOGY, Distribution.)

Because of the potential for unknown effects from trovafloxacin in nursing infants from mothers taking trovafloxacin, a decision should be made either to discontinue nursing or to discontinue the drug, taking into account the importance of the drug to the mother.

Pediatric Use

The safety and effectiveness of trovafloxacin in pediatric patients and adolescents less than 18 years of age have not been established. Quinolones, including trovafloxacin, cause arthropathy and osteochondrosis in juvenile animals of several species. (See WARNINGS.)

Geriatric Use

In multiple-dose clinical trials of trovafloxacin, 27% of patients were ≥65 years of age and 12% of patients were ≥75 years of age. The overall incidence of drug-related adverse reactions, including central nervous system and gastrointestinal side effects, was less in the ≥65 year group than the other age groups.

ADVERSE REACTIONS

Over 6000 patients have been treated with TROVAN in multidose clinical efficacy trials worldwide.

In TROVAN studies the majority of adverse reactions were described as mild in nature (over 90% were described as mild or moderate). TROVAN was discontinued for adverse events thought related to drug in 5% of patients (dizziness 2.4%, nausea 1.9%, headache 1.1%, and vomiting 1.0%).

TROVAN Drug-Related Adverse Reactions (frequency ≥1%) in Multiple-Dose Clinical Trials
 |  | 200 mg oral qd (N=3259) | 200 mg I.V.→ 200 mg oral qd (N=634) | 300 mg I.V.→ 200 mg oral qd (N=623)
Dizziness |  | 11% | 2% | 2%
Lightheadedness |  | 4% | 2% | <1%
Nausea |  | 8% | 5% | 4%
Headache |  | 5% | 5% | 1%
Vomiting |  | 3% | 1% | 3%
Diarrhea |  | 2% | 2% | 2%
Abdominal pain |  | 1% | 1% | 0%
Application/
injection/insertion site |  | n/a | 5% | 2%
reaction/
Vaginitis |  | 2% | 2% | <1%
Pruritus |  | <1% | 2% | 2%
Rash |  | <1% | 2% | 2%

Dizziness/lightheadedness on TROVAN is generally mild, lasts for a few hours following a dose, and in most cases, resolves with continued dosing. The incidence of dizziness and lightheadedness in TROVAN patients over 65 years is 3.1% and 0.6%, respectively. (See PRECAUTIONS: Information for Patients.)

TROVAN appears to have a low potential for phototoxicity. In clinical trials with TROVAN, only mild, treatment-related phototoxicity was observed in less than 0.03% (2/7096) of patients.

Additional reported drug-related events in clinical trials (remotely, possibly, probably or unknown) that occurred in <1% of TROVAN-treated patients are:

APPLICATION/INJECTION/INSERTION SITE: Application/injection/insertion site device complications, inflammation, pain, edema

AUTONOMIC NERVOUS: flushing, increased sweating, dry mouth, cold clammy skin, increased saliva

CARDIOVASCULAR: peripheral edema, chest pain, thrombophlebitis, hypotension, palpitation, periorbital edema, hypertension, syncope, tachycardia, angina pectoris, bradycardia, peripheral ischemia, edema, dizziness postural

CENTRAL & PERIPHERAL NERVOUS SYSTEM: confusion, paresthesia, vertigo, hypoesthesia, ataxia, convulsions, dysphonia, hypertonia, migraine, involuntary muscle contractions, speech disorder, encephalopathy, abnormal gait, hyperkinesia, hypokinesia, tongue paralysis, abnormal coordination, tremor, dyskinesia

GASTROINTESTINAL: altered bowel habit, constipation, diarrhea-Clostridium difficile, dyspepsia, flatulence, loose stools, gastritis, dysphagia, increased appetite, gastroenteritis, rectal disorder, colitis, pseudomembranous colitis, enteritis, eructation, gastrointestinal disorder, melena, hiccup

ORAL CAVITY: gingivitis, stomatitis, altered saliva, tongue disorder, tongue edema, tooth disorder, cheilitis, halitosis

GENERAL/OTHER: fever, fatigue, pain, asthenia, moniliasis, hot flushes, back pain, chills, infection (bacterial, fungal), malaise, sepsis, alcohol intolerance, allergic reaction, anaphylactoid reaction, drug (other) toxicity/reaction, weight increase, weight decrease

HEMATOPOIETIC: anemia, granulocytopenia, hemorrhage unspecified, leukopenia, prothrombin decreased, thrombocythemia, thrombocytopenia

LIVER/BILIARY: increased hepatic enzymes, hepatic function abnormal, bilirubinemia, discolored feces, jaundice

METABOLIC/NUTRITIONAL: hyperglycemia, thirst

MUSCULOSKELETAL: arthralgia, muscle cramps, myalgia, muscle weakness, skeletal pain, tendinitis, arthropathy

PSYCHIATRIC: anxiety, anorexia, agitation, nervousness, somnolence, insomnia, depression, amnesia, concentration impaired, depersonalization, dreaming abnormal, emotional lability, euphoria, hallucination, impotence, libido decreased-male, paroniria, thinking abnormal

REPRODUCTIVE: Female: leukorrhea, menstrual disorder; Male: balanoposthitis

RESPIRATORY: dyspnea, rhinitis, sinusitis, bronchospasm, coughing, epistaxis, respiratory insufficiency, upper respiratory tract infection, respiratory disorder, asthma, hemoptysis, hypoxia, stridor

SKIN/APPENDAGES: pruritus ani, skin disorder, skin ulceration, angioedema, dermatitis, dermatitis fungal, photosensitivity skin reaction, seborrhea, skin exfoliation, urticaria

SPECIAL SENSES: taste perversion, eye pain, abnormal vision, conjunctivitis, photophobia, conjuctival hemorrhage, hyperacusis, scotoma, tinnitus, visual field defect, diplopia, xerophthalmia

URINARY SYSTEM: dysuria, face edema, micturition frequency, interstitial nephritis, renal failure acute, renal function abnormal, urinary incontinence

LABORATORY CHANGES: Changes in laboratory parameters, without regard to drug relationship, occurring in ≥1% of TROVAN-treated patients were: decreased hemoglobin and hematocrit; increased platelets; decreased and increased WBC; eosinophilia; increased ALT (SGPT), AST (SGOT), and alkaline phosphatase; decreased protein and albumin; increased BUN and creatinine; decreased sodium; and bicarbonate. It is not known whether these abnormalities were caused by the drug or the underlying condition being treated.

The incidence and magnitude of liver function abnormalities with TROVAN were the same as comparator agents except in the only study in which oral TROVAN was administered for 28 days. In this study (chronic bacterial prostatitis) nine percent (13/140) of TROVAN-treated patients experienced elevations of serum transaminases (AST and/or ALT) of ≥3 times the upper limit of normal. These liver function test abnormalities generally developed at the end of, or following completion of, the planned 28-day course of therapy, but were not associated with concurrent elevations of related laboratory measures of hepatic function (such as serum bilirubin, alkaline phosphatase, or lactate dehydrogenase). Patients were asymptomatic with these abnormalities, which generally returned to normal within 1–2 months after discontinuation of therapy. (See ADVERSE REACTIONS: POST-MARKETING EXPERIENCE subsection.)

POST-MARKETING EXPERIENCE

Adverse reactions reported with TROVAN during the post-marketing period include:

GASTROINTESTINAL: symptomatic pancreatitis.

GENERAL/OTHER: anaphylaxis, Stevens-Johnson Syndrome.

HEMATOPOIETIC: agranulocytosis, aplastic anemia, pancytopenia.

LIVER/BILIARY: symptomatic hepatitis (some patients experienced an associated peripheral eosinophilia), liver failure (including acute hepatic necrosis with eosinophilic infiltration). TROVAN-associated liver enzyme abnormalities and/or symptomatic hepatitis have occurred during short-term or long-term therapy. (See WARNINGS.)

OVERDOSAGE

Trovafloxacin has a low order of acute toxicity. The minimum lethal oral dose in mice and rats was 2000 mg/kg or greater. The minimum lethal I.V. dose for the prodrug, alatrofloxacin, was 50–125 mg/kg for mice and greater than 75 mg/kg for rats. Clinical signs observed included decreased activity and respiration, ataxia, ptosis, tremors and convulsions.

In the event of acute oral overdosage, the stomach should be emptied by inducing vomiting or by gastric lavage. The patient should be carefully observed and given symptomatic and supportive treatment. Adequate hydration should be maintained. Trovafloxacin is not efficiently removed from the body by hemodialysis.

DOSAGE AND ADMINISTRATION

The recommended dosage for TROVAN for the treatment of serious, life- or limb-threatening infections is described in the table below. Doses of TROVAN are administered once every 24 hours. TROVAN should not usually be administered for more than 2 weeks. It should only be administered for longer than 2 weeks if the treating physician believes the benefits to the individual patients clearly outweigh the risks of such longer-term treatment. (See boxed WARNING.)

Oral doses should be administered at least 2 hours before or 2 hours after antacids containing magnesium or aluminum, as well as sucralfate, citric acid buffered with sodium citrate (e.g., Bicitra®), metal cations (e.g., ferrous sulfate) and Videx®, (Didanosine), chewable/buffered tablets or the pediatric powder for oral solution.

Intravenous morphine should be administered at least 2 hours after oral TROVAN dosing in the fasted state and at least 4 hours after oral TROVAN is taken with food.

Patients whose therapy is started with TROVAN I.V. may be switched to TROVAN Tablets to complete the course of therapy, if deemed appropriate by the treating physician. In certain patients with serious and life- or limb-threatening infections as described in the INDICATIONS AND USAGE Section, TROVAN Tablets may be considered appropriate initial therapy, when the treating physician believes that the benefit of the product for the patient outweighs the potential risk.

TROVAN I.V. (alatrofloxacin mesylate injection) should only be administered by INTRAVENOUS infusion. It is not for intramuscular, intrathecal, intraperitoneal, or subcutaneous administration.

Single-use vials require dilution prior to administration. (See PREPARATION OF ALATROFLOXACIN MESYLATE INJECTION FOR ADMINISTRATION.)

DOSAGE GUIDELINES
INFECTION [due to the designated pathogens (See INDICATIONS AND USAGE.)] /LOCATION AND TYPE | DAILY UNIT DOSE AND ROUTE OF ADMINISTRATION | TOTAL DURATION (See WARNINGS.)
Nosocomial Pneumonia (See NOTE 1 below.) | 300 mg I.V. [Where the 300 mg TROVAN I.V. dose is indicated, therapy should be decreased to the 200 mg dose as soon as clinically indicated.] followed by 200 mg oral | 10–14 days
Community Acquired Pneumonia | 200 mg oral or 200 mg I.V. followed by 200 mg oral | 7–14 days
Complicated Intra-Abdominal Infections, including post-surgical infections | 300 mg I.V. followed by 200 mg oral | 7–14 days
Gynecologic and Pelvic Infections | 300 mg I.V. followed by 200 mg oral | 7–14 days
Skin and Skin Structure Infections, Complicated, including diabetic foot infections | 200 mg oral or 200 mg I.V. followed by 200 mg oral | 10–14 days

NOTE: As with other antimicrobials, where Pseudomonas aeruginosa is a documented or presumptive pathogen, combination therapy with either an aminoglycoside or aztreonam may be clinically indicated.

IMPAIRED RENAL FUNCTION: No adjustment in the dosage of TROVAN is necessary in patients with impaired renal function. Trovafloxacin is eliminated primarily by biliary excretion. Trovafloxacin is not efficiently removed from the body by hemodialysis.

CHRONIC HEPATIC DISEASE (cirrhosis): The following table provides dosing guidelines for patients with mild or moderate cirrhosis (Child-Pugh Class A and B). There are no data in patients with severe cirrhosis (Child-Pugh Class C).

INDICATED DOSE (Normal hepatic function) | CHRONIC HEPATIC DISEASE DOSE
300 mg I.V. | 200 mg I.V.
200 mg I.V. or oral | 100 mg I.V. or oral

INTRAVENOUS ADMINISTRATION

AFTER DILUTION WITH AN APPROPRIATE DILUENT, TROVAN I.V. SHOULD BE ADMINISTERED BY INTRAVENOUS INFUSION OVER A PERIOD OF 60 MINUTES. CAUTION: RAPID OR BOLUS INTRAVENOUS INFUSION SHOULD BE AVOIDED. (See PRECAUTIONS.)

TROVAN I.V. is supplied in single-use vials containing a concentrated solution of alatrofloxacin mesylate in Water for Injection (equivalent of 200 mg or 300 mg as trovafloxacin). Each mL contains alatrofloxacin mesylate equivalent to 5 mg trovafloxacin. (See HOW SUPPLIED for container sizes.) THESE TROVAN I.V. SINGLE-USE VIALS MUST BE FURTHER DILUTED WITH AN APPROPRIATE SOLUTION PRIOR TO INTRAVENOUS ADMINISTRATION. This parenteral drug product should be inspected visually for discoloration and particulate matter prior to dilution and administration. Since no preservative or bacteriostatic agent is present in this product, aseptic technique must be used in preparation of the final parenteral solution.

PREPARATION OF ALATROFLOXACIN MESYLATE INJECTION FOR ADMINISTRATION

The intravenous dose should be prepared by aseptically withdrawing the appropriate volume of concentrate from the vials of TROVAN I.V. This should be diluted with a suitable intravenous solution to a final concentration of 1–2 mg/mL. (SeeCompatible Intravenous Solutions.) The resulting solution should be infused over a period of 60 minutes by direct infusion or through a Y-type intravenous infusion set which may already be in place.

Since the vials are for single-use only, any unused portion should be discarded.

Since only limited data are available on the compatibility of alatrofloxacin intravenous injection with other intravenous substances, additives or other medications should not be added to TROVAN I.V. in single-use vials or infused simultaneously through the same intravenous line.

If the same intravenous line is used for sequential infusion of several different drugs, the line should be flushed before and after infusion of TROVAN I.V. with an infusion solution compatible with TROVAN I.V. and with any other drug(s) administered via this common line.

If TROVAN I.V. is to be given concomitantly with another drug, each drug should be given separately in accordance with the recommended dosage and route of administration for each drug.

The desired dosage of TROVAN I.V. may be prepared according to the following chart:

DOSAGE STRENGTH (mg) (trovafloxacin equivalent) | VOLUME TO WITHDRAW (mL) | DILUENT VOLUME (mL) | TOTAL VOLUME (mL | INFUSION CONC (mg/mL)
100 mg | 20 | 30 | 50 | 2
100 mg | 20 | 80 | 100 | 1
200 mg | 40 | 60 | 100 | 2
200 mg | 40 | 160 | 200 | 1
300 mg | 60 | 90 | 150 | 2
300 mg | 60 | 240 | 300 | 1

For example, to prepare a 200 mg dose at an infusion concentration of 2 mg/mL (as trovafloxacin), 40 mL of TROVAN I.V. is withdrawn from a vial and diluted with 60 mL of a compatible intravenous fluid to produce a total infusion solution volume of 100 mL.

Compatible Intravenous Solutions

5% Dextrose Injection, USP
0.45% Sodium Chloride Injection, USP
5% Dextrose and 0.45% Sodium Chloride Injection, USP
5% Dextrose and 0.2% Sodium Chloride Injection, USP
Lactated Ringer's and 5% Dextrose Injection, USP

TROVAN I.V. should not be diluted with 0.9% Sodium Chloride Injection, USP (normal saline), alone or in combination with other diluents. A precipitate may form under these conditions. In addition, TROVAN I.V. should not be diluted with Lactated Ringer's, USP.

Normal saline, 0.9% Sodium Chloride Injection, USP can be used for flushing I.V. lines prior to or after administration of TROVAN I.V.

Stability of TROVAN I.V. as Supplied

When stored under recommended conditions, TROVAN I.V., as supplied in 40 mL or 60 mL vials, is stable through the expiration date printed on the label.

Stability of TROVAN I.V. Following Dilution

TROVAN I.V., when diluted with compatible intravenous solutions to concentrations of 0.5 to 2.0 mg/mL (as trovafloxacin), is physically and chemically stable for up to 7 days when refrigerated or up to 3 days at room temperature stored in glass bottles or plastic (PVC type) intravenous containers.

HOW SUPPLIED

Trovan Tablets and Injection are being distributed only to hospitals and long term nursing care facilities for patients initiating therapy in these facilities

Tablets

TROVAN (trovafloxacin mesylate) Tablets are available as blue, film-coated tablets. The 100 mg tablets are round and contain trovafloxacin mesylate equivalent to 100 mg trovafloxacin. The 200 mg tablets are modified oval-shaped and contain trovafloxacin mesylate equivalent to 200 mg trovafloxacin.

TROVAN Tablets are packaged and in unit dose blister strips in the following configurations:

100-mg tablets: color: blue; shape: round; debossing: "PFIZER" on one side and "378" on the other
Bottles of 30 (NDC 0049-3780-30)
Unit Dose/40 tablets (NDC 0049-3780-43)

200-mg tablets: color: blue; shape: modified oval; debossing: "PFIZER" on one side and "379" on the other
Bottles of 30 (NDC 0049-3790-30)
Unit Dose/40 tablets (NDC 0049-3790-43)

Storage

TROVAN Tablets should be stored at 15°C to 30°C (59°F to 86°F) in airtight containers (USP).

Injection

TROVAN is also available for intravenous administration as the prodrug, TROVAN I.V. (alatrofloxacin mesylate injection), in the following configurations:

Single-use vials containing a clear, colorless to pale-yellow concentrated solution of alatrofloxacin mesylate equivalent to 5 mg trovafloxacin/mL.

5 mg/mL, 40 mL, 200 mg
Unit dose package (NDC 0049-3890-28)

5 mg/mL, 60 mL, 300 mg
Unit dose package (NDC 0049-3900-28)

Storage

TROVAN I.V. should be stored at 15°C to 30°C (59°F to 86°F). Protect From Light. Do Not Freeze.

ANIMAL PHARMACOLOGY

Quinolones have been shown to cause arthropathy in immature animals.

Arthropathy and chondrodysplasia were observed in immature animals given trovafloxacin. (See WARNINGS.)

At doses from 10 to 15 times the human dose based on mg/kg or approximately 3 to 5 times based on mg/m^2, trovafloxacin has been shown to cause arthropathy in immature rats and dogs. In addition, these drugs are associated with an increased incidence of chondrodysplasia in rats compared to controls. There is no evidence of arthropathies in fully mature rats and dogs at doses from 40 or 10 times the human dose based on mg/kg or approximately 5 times based on mg/m^2 for a 6 month exposure period.

Unlike some other members of the quinolone class, crystalluria and ocular toxicity were not observed in chronic safety studies with rats or dogs with either trovafloxacin or its prodrug, alatrofloxacin.

Quinolones have been reported to have proconvulsant activity that is exacerbated with concomitant use of non-steroidal anti-inflammatory drugs (NSAIDS). Neither trovafloxacin administered orally at 500 mg/kg, nor alatrofloxacin administered intravenously at 75 mg/kg, showed an increase in measures of seizure activity in mice at doses when used in combination with the active metabolite of the NSAID, fenbufen.

As with other members of the quinolone class, trovafloxacin at doses 5 to 10 times the human dose based on mg/kg or 1 to 5 times the human dose based on mg/m^2 produces testicular degeneration in rats and dogs dosed for 6 months.

At a dose of trovafloxacin 10 times the highest human dose based on mg/kg or approximately 5 times based on mg/m^2, elevated liver enzyme levels which correlated with centrilobular hepatocellular vacuolar degeneration and necrosis were observed in dogs in a 6 month study. A subsequent study demonstrated reversibility of these effects when trovafloxacin was discontinued.

CLINICAL STUDIES

Hospitalized Community Acquired Pneumonia

Adult patients with clinically and radiologically documented community acquired pneumonia, requiring hospitalization and initial intravenous therapy, participated in two randomized, multicenter, double-blind, double-dummy trials. The first trial compared intravenous alatrofloxacin (200 mg once daily for 2 to 7 days) followed by oral trovafloxacin (200 mg once daily) for a total of 7 to 14 days of therapy to intravenous ciprofloxacin (400 mg BID) plus ampicillin (500 mg QID) for 2 to 7 days followed by oral ciprofloxacin (500 mg BID) plus amoxicillin (500 mg TID) for a total of 7 to 14 days of therapy. The second study compared intravenous alatrofloxacin (200 mg once daily for 2 to 7 days) followed by oral trovafloxacin (200 mg once daily) for a total of 7 to 14 days of therapy to intravenous ceftriaxone (1000 mg once daily for 2 to 7 days) followed by oral cefpodoxime (400 mg BID) for 7 to 14 days of total therapy with optional blinded erythromycin added to the ceftriaxone/cefpodoxime arm if an atypical pneumonia was suspected.

The clinical success rate (cure + improvement with no need for further antibiotic therapy) at the End of Treatment was 90% (311/346) and 90% (325/363) for TROVAN and the comparator agents, respectively. The clinical success rate at the End of Study (Day 30) was 86% (256/299) and 85% (283/334) for TROVAN and the comparator agents, respectively. All cause mortality (Day 1–35) was 2.45% (10/408) on TROVAN and 5.45% (23/422) on the comparator agents.

The following outcomes are the clinical success rates for the clinically evaluable patient groups by pathogen in these two studies:

 | End of Treatment |  | End of Study
Pathogen | TROVAN | Comparators | TROVAN | Comparators
S. pneumoniae | 89% (63/71) | 95% (62/65) | 87% (55/63) | 91% (50/55)
H. influenzae | 97% (35/36) | 94% (46/49) | 90% (28/31) | 94% (44/47)
M. catarrhalis | 100% (8/8) | 100% (4/4) | 100% (6/6) | 100% (4/4)
S. aureus | 100% (8/8) | 93% (13/14) | 100% (6/6) | 91% (10/11)
K. pneumoniae | 100% (3/3) | 89% (8/9) | 100% (3/3) | 86% (6/7)
L. pneumophila | 77% (10/13) | 86% (12/14) | 75% (9/12) | 86% (12/14)
M. pneumoniae | 100% (20/20) | 87% (13/15) | 94% (17/18) | 79% (11/14)
C. pneumoniae | 75% (6/8) | 100% (18/18) | 67% (4/6) | 94% (16/17)

Of the above patients with clinical failure at end of treatment or study, only one alatrofloxacin patient (H. influenzae + S. pneumoniae) and one ceftriaxone + erythromycin patient (Legionella) had a microbiologically confirmed persistent pathogen at the time of failure with no emergence of resistance in either study.

Nosocomial Pneumonia

Adult patients with clinically and radiologically documented nosocomial pneumonia participated in a randomized, multicenter, double-blind, double-dummy trial comparing intravenous alatrofloxacin (300 mg once daily for 2 to 7 days) followed by oral trovafloxacin (200 mg once daily) for a total of 7 to 14 days of therapy to intravenous ciprofloxacin (400 mg BID) for 2 to 7 days followed by oral ciprofloxacin (750 mg BID) for a total of 7 to 14 days of therapy with optional blinded clindamycin or metronidazole added to the ciprofloxacin arm if an anaerobic pneumonia was suspected. In subjects with documented Pseudomonas infection or methicillin-resistant S. aureus, aztreonam or vancomycin, respectively, could have been added to either treatment regimen.

The clinical success rate (cure + improvement with no need for further antibiotic therapy) at the End of Treatment was 77% (68/88) and 78% (79/101) for TROVAN and ciprofloxacin, respectively. The clinical success rate at the End of Study (Day 30) was 69% (50/72) and 68% (54/79) for TROVAN and ciprofloxacin, respectively.

The following outcomes are the clinical success rates for the clinically evaluable patient groups by pathogen:

 | End of Treatment |  | End of Study
Pathogen | TROVAN | Ciprofloxacin | TROVAN | Ciprofloxacin
P. aeruginosa | 67% (10/15) | 55% (6/11) | 62% (8/13) | 25% (2/8)
H. influenzae | 88% (7/8) | 89% (8/9) | 83% (5/6) | 86% (6/7)
E. coli | 71% (5/7) | 80% (4/5)) | 50% (3/6) | 80% (4/5)
S. aureus | 64% (7/11) | 80% (8/10) | 50% (4/8) | 67% (4/6)

Of the above patients with clinical failure at end of treatment or study, 2 alatrofloxacin patients (S. aureus, P. aeruginosa) and 4 ciprofloxacin patients (all P. aeruginosa) had a microbiologically confirmed persistent pathogen at the time of failure. Three of the 4 ciprofloxacin patients with clinical failure and persistence had emergence of resistance with none on alatrofloxacin.

Complicated Intra-Abdominal Infections

Patients hospitalized with clinically documented, complicated intra-abdominal infections, including post-surgical infections, participated in a randomized, double-blind, multicenter trial comparing intravenous alatrofloxacin (300 mg once daily) followed by oral trovafloxacin (200 mg once daily) to intravenous imipenem/cilastatin (1g q8h) followed by oral amoxicillin/clavulanic acid (500 mg TID) for a maximum of 14 days of therapy. The clinical success rate (cure + improvement) at the End of Treatment was 88% (136/155) and 86% (122/142) for alatrofloxacin→trovafloxacin and imipenem/cilastatin→amoxicillin/clavulanic acid, respectively. The clinical success rate at the End of Study (Day 30) was 83% (129/156) and 84% (127/152) for alatrofloxacin→trovafloxacin and imipenem/cilastatin→amoxicillin/clavulanic acid, respectively.

The following are the clinical success rates for the clinically evaluable patient groups by pathogen:

 | End of Treatment |  | End of Study
Pathogen | TROVAN | Imipenem/Cila Amox/Clav | TROVAN | Imipenem/Cila Amox/Clav
E. coli | 94% (72/77) | 90% (52/58) | 86% (66/77) | 86% (51/59)
Bacteroides fragilis | 97% (30/31) | 82% (28/34) | 84% (26/31) | 75% (27/36)
viridans group streptococci | 90% (18/20) | 83% (19/23) | 90% (18/20) | 78% (18/23)
Pseudomonas aeruginosa | 94% (15/16) | 82% (14/17) | 88% (14/16) | 83% (15/18)
Klebsiella pneumoniae | 80% (12/15) | 71% (10/14) | 67% (10/15) | 71% (10/14)
Peptostreptococcus spp. | 86% (12/14) | 88% (7/8) | 79% (11/14) | 75% (6/8)
Prevotella spp. | 77% (10/13) | 50% (2/4) | 77% (10/13) | 60% (3/5)

Of patients with a baseline pathogen and a clinical response of failure at the End of Study, 9 of 26 on TROVAN and 10 of 21 on imipenem/cilastatin had microbiologically-confirmed persistence of the baseline pathogen with no emergence of resistance in either group.

REFERENCES

1. National Committee for Clinical Laboratory Standards, Methods for Dilution Antimicrobial Susceptibility Tests for Bacteria That Grow Aerobically – Fourth Edition; Approved Standard, NCCLS Document M7-A4, Vol. 17, No. 2, NCCLS, Wayne, PA, January, 1997.
2. National Committee for Clinical Laboratory Standards. Performance Standards for Antimicrobial Disk Susceptibility Tests – Sixth Edition; Approved Standard, NCCLS Document M2-A6, Vol. 17, No. 1, NCCLS, Wayne, PA, January, 1997.
3. National Committee for Clinical Laboratory Standards. Methods for Antimicrobial Susceptibility Testing of Anaerobic Bacteria – Fourth Edition; Approved Standard, NCCLS Document M11-A4, Vol. 17, No. 22, NCCLS, Wayne, PA, December, 1997.

Rx only

70-5328-00-6
April 2000